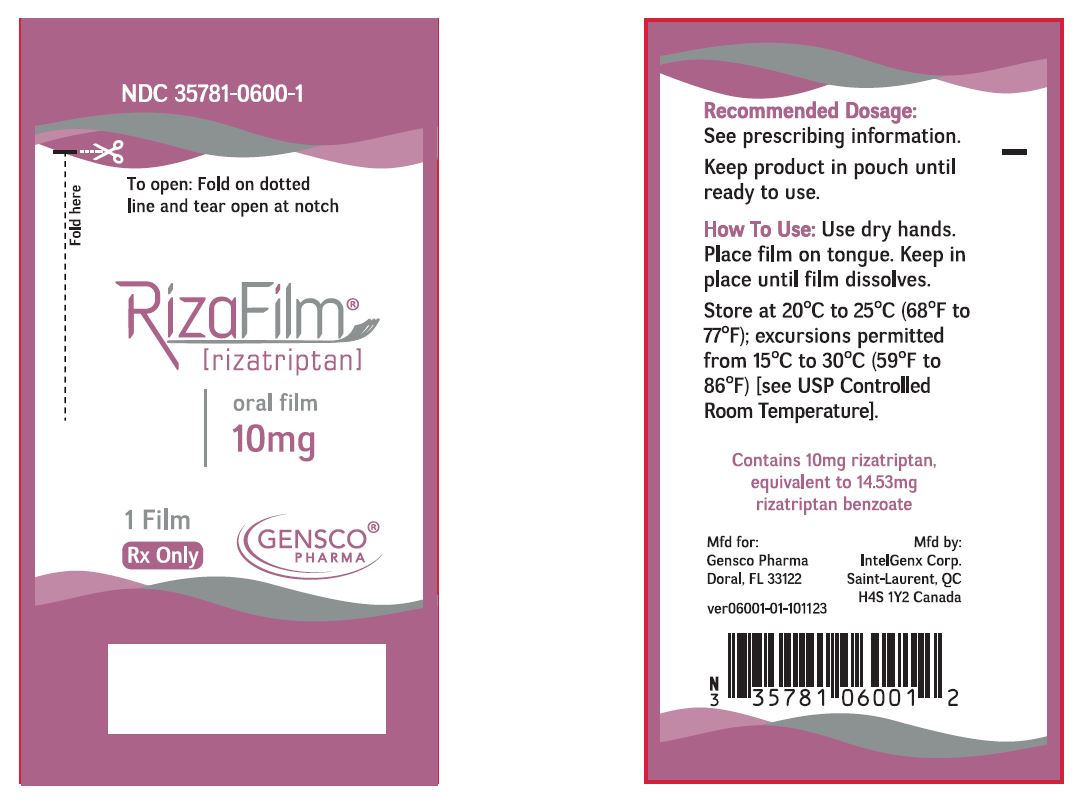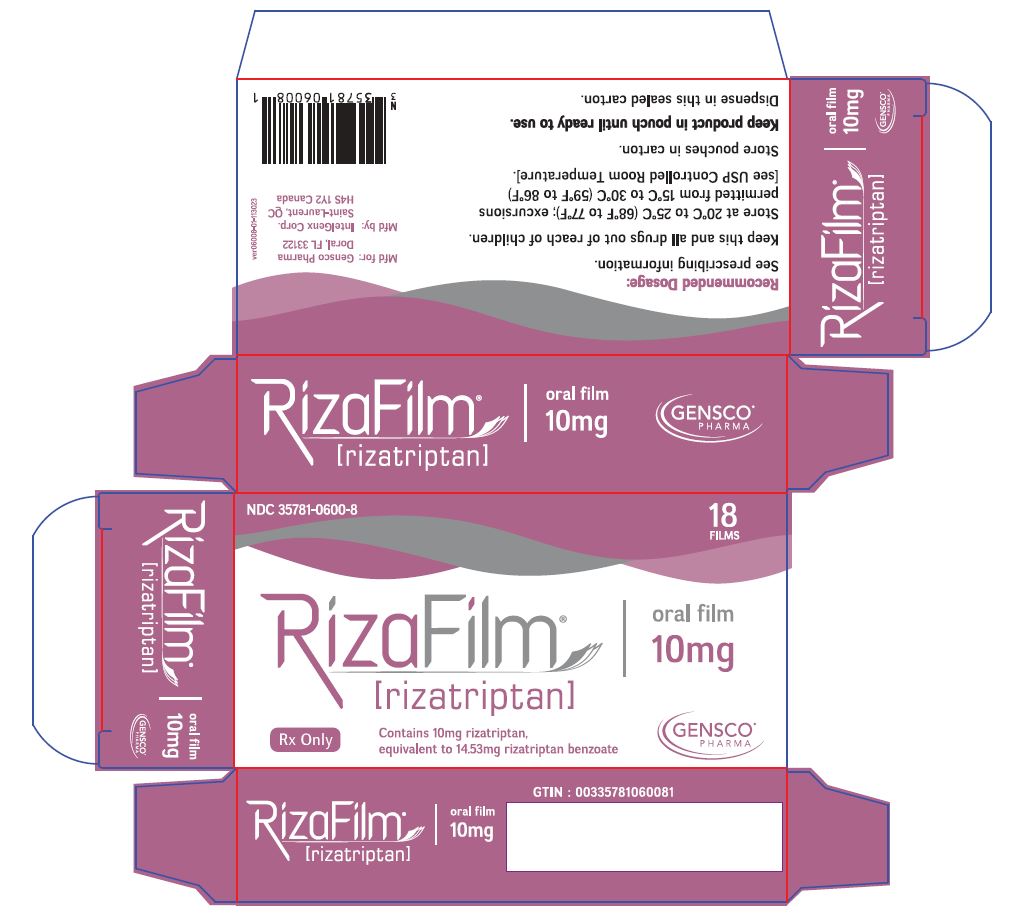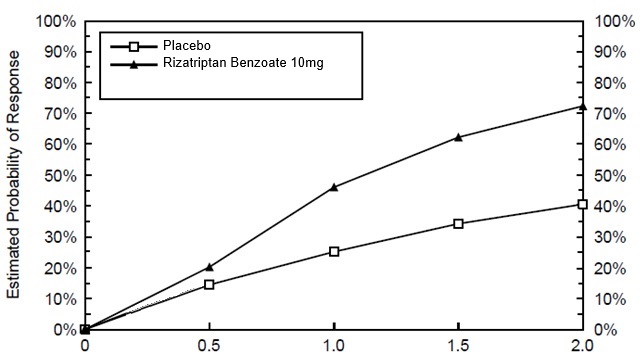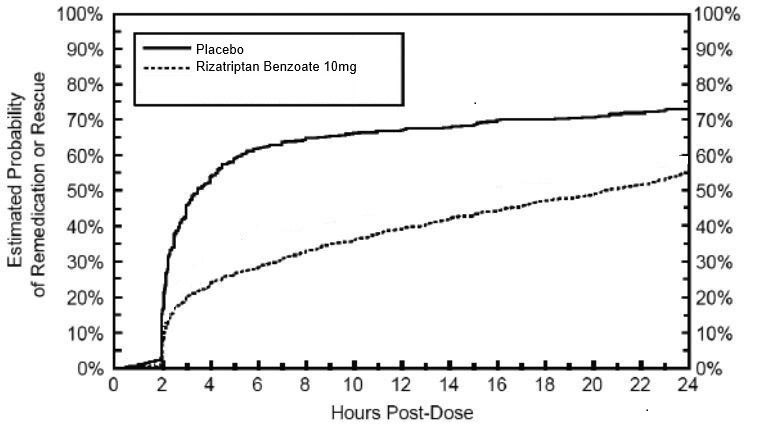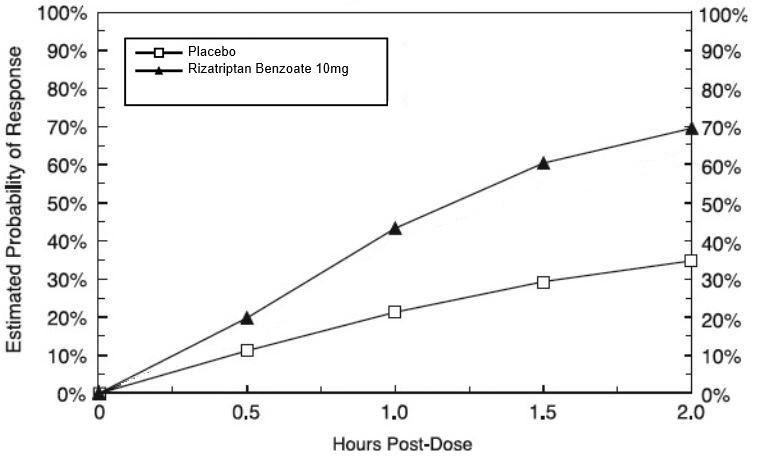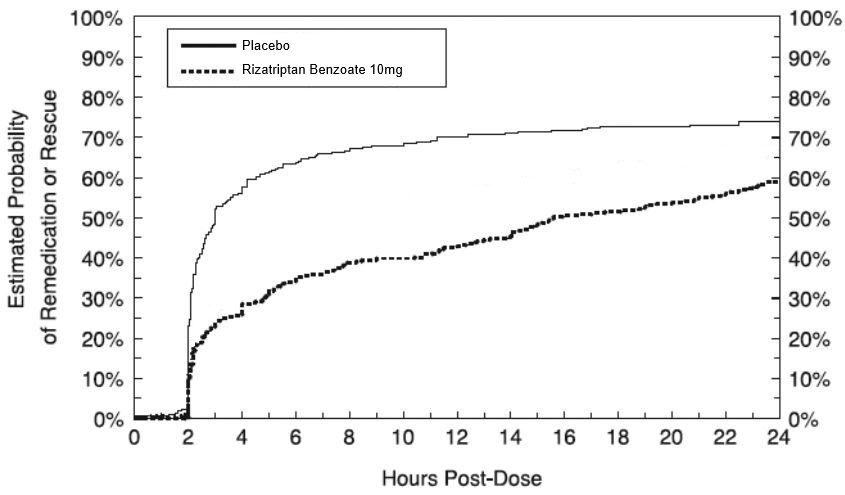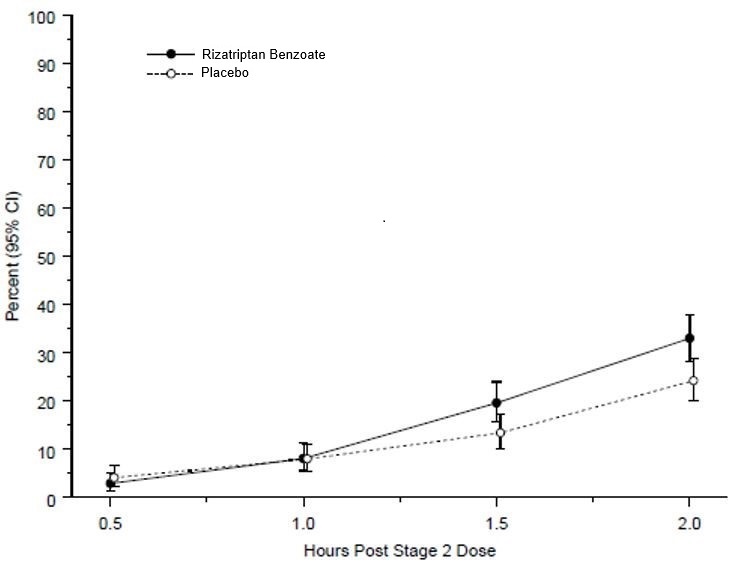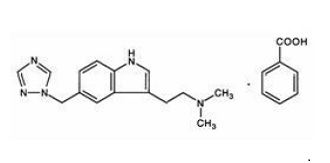 DRUG LABEL: RIZAFILM
NDC: 35781-0600 | Form: FILM
Manufacturer: Gensco Laboratories LLC
Category: prescription | Type: HUMAN PRESCRIPTION DRUG LABEL
Date: 20240110

ACTIVE INGREDIENTS: RIZATRIPTAN BENZOATE 10 mg/1 1
INACTIVE INGREDIENTS: SUCRALOSE; LEVOMENTHOL; TRIACETIN; AMMONIUM GLYCYRRHIZATE; COPOVIDONE; HYDROXYPROPYL CELLULOSE (90000 WAMW); TITANIUM DIOXIDE; BUTYLATED HYDROXYTOLUENE; ISOPROPYL ALCOHOL; METHYL ETHYL KETONE; ETHYLCELLULOSE, UNSPECIFIED; SODIUM ACETATE; FD&C BLUE NO. 1; CUPRIC CHLORIDE

HIGHLIGHTS OF PRESCRIBING INFORMATION

These highlights do not include all the information needed to use RIZAFILM safely and effectively. See full prescribing information for RIZAFILM. RIZAFILM (rizatriptan) oral film
Initial U.S. Approval: 1998

1 INDICATIONS AND USAGE

RizaFilm is a serotonin (5-HT) 1B/1D receptor agonist (triptan) indicated for the acute treatment of migraine with or without aura in adults and in pediatric patients 12 to 17 years of age weighing 40 kg or more (1)

Limitations of Use:

- Use only after a clear diagnosis of migraine has been established (1)
- Not indicated for the preventive treatment of migraine (1)
- Not indicated for the treatment of cluster headache (1)

2 DOSAGE AND ADMINISTRATION

- RizaFilm is administered on the tongue (2.1)
- Adults: 10 mg single dose; separate repeat doses by at least two hours; maximum cumulative dosage in a 24-hour period is 30 mg (2.1)
- Pediatric patients 12 to 17 years of age weighing 40 kg or more: 10 mg single dose (2.2)

3 DOSAGE FORMS AND STRENGTHS

- Oral film: 10 mg rizatripan. (3)

4 CONTRAINDICATIONS

- History of ischemic heart disease or coronary artery vasospasm (4)
- History of stroke or transient ischemic attack (4)
- Wolff-Parkinson-White syndrome or other cardiac accessory conduction pathway disorders (4)
- Peripheral vascular disease (4)
- Ischemic bowel disease (4)
- Uncontrolled hypertension (4)
- Recent (within 24 hours) use of another 5-HT1 agonist (e.g., another triptan), or of an ergotamine-containing medication (4)
- Hemiplegic or basilar migraine (4)
- MAO-A inhibitor used in the past 2 weeks (4)
- Co-administration with propranolol (4)
- Hypersensitivity to rizatriptan or any of the ingredients of RizaFilm (4)

5 WARNINGS AND PRECAUTIONS

- Myocardial ischemia, myocardial infarction, and Prinzmetal's angina: Perform cardiac evaluation in patients with multiple cardiovascular risk factors (5.1)
- Arrhythmias: Discontinue dosing if occurs (5.2)
- Chest/throat/neck/jaw pain, tightness, pressure, or heaviness; Generally not associated with myocardial ischemia; Evaluate patients at high risk (5.3)
- Cerebral hemorrhage, subarachnoid hemorrhage, and stroke: Discontinue dosing if occurs (5.4)
- Gastrointestinal ischemic events, peripheral vasospastic reactions: Discontinue dosing if occurs (5.5)
- Hypersensitivity Reactions: angioedema and anaphylaxis have occurred (5.6)
- Medication overuse headache: Detoxification may be necessary (5.7)
- Serotonin syndrome: Discontinue dosing if occurs (5.8)

6 ADVERSE REACTIONS

The most common adverse reactions in adults were (incidence ≥5% and greater than placebo): asthenia/fatigue, somnolence, pain/pressure sensation, dizziness, and nausea (6.1) To report SUSPECTED ADVERSE REACTIONS, contact Gensco Pharma at 1-866-608-6284 or FDA at 1-800-FDA-1088 or www.fda.gov/medwatch

8 USE IN SPECIFIC POPULATIONS

- Pregnancy: Based on animal data, may cause fetal harm (8.1)

FULL PRESCRIBING INFORMATION

1 INDICATIONS AND USAGE

RizaFilm™ is indicated for the acute treatment of migraine with or without aura in adults and in pediatric patients 12 to 17 years of age weighing 40 kg or more.

Limitations of Use

- RizaFilm should only be used where a clear diagnosis of migraine has been established. If a patient has no response for the first migraine attack treated with RizaFilm, the diagnosis of migraine should be reconsidered before RizaFilm is administered to treat any subsequent attacks.
- RizaFilm is not indicated for the preventive treatment of migraine.
- Safety and effectiveness of RizaFilm have not been established for cluster headache.

2 DOSAGE AND ADMINISTRATION

2.1 Dosing Information in Adults

The recommended dose of RizaFilm in adults is 10 mg administered on the tongue. The maximum cumulative dose that may be given in 24 hours is 30 mg, with doses separated by at least 2 hours. The safety of treating, on average, more than four headaches in a 30-day period has not been established.

2.2 Dosing Information in Pediatric Patients (12 to 17 Years of Age)

The recommended dose of RizaFilm in patients weighing 40 kg or more is 10 mg administered on the tongue.

The efficacy and safety of treatment with more than one dose of RizaFilm within 24 hours in pediatric patients 12 to 17 years of age have not been established.

2.3 Administration of RizaFilm Oral Films

For RizaFilm oral films, administration with liquid is not necessary. Oral films are packaged individually in child-resistant aluminum pouches with a tear notch. To open the pouch, fold on the dotted line and tear open at the notch. Place the oral film on the tongue, where it will disintegrate within approximately two minutes and can be swallowed with saliva.

3 DOSAGE FORMS AND STRENGTHS

RizaFilm 10 mg oral films are white to off-white, rectangular strips of 2.2 cm x 2.75 cm with a blue identifier “RIZA10” on one side.

4 CONTRAINDICATIONS

RizaFilm is contraindicated in patients with:

- Ischemic coronary artery disease (angina pectoris, history of myocardial infarction, or documented silent ischemia), or other significant underlying cardiovascular disease [ see Warnings and Precautions (5.1) ].
- Coronary artery vasospasm including Prinzmetal's angina[ see Warnings and Precautions (5.1) ].
- Wolff-Parkinson-White Syndrome or arrhythmias associated with other cardiac accessory conduction pathway disorders [see Warnings and Precautions (5.2) ]
- History of stroke or transient ischemic attack (TIA) [ see Warnings and Precautions (5.4) ].
- Peripheral vascular disease (PVD) [ see Warnings and Precautions (5.5) ].
- Ischemic bowel disease [ see Warnings and Precautions (5.5) ].
- Uncontrolled hypertension [ see Warnings and Precautions (5.9) ].
- Recent use (i.e., within 24 hours) of another 5-HT1 agonist, ergotamine-containing medication, or ergot-type medication (such as dihydroergotamine or methysergide) [ see Drug Interactions (7.2 and 7.3) ].
- Hemiplegic or basilar migraine.
- Concurrent administration or recent discontinuation (i.e., within 2 weeks) of a MAO-A inhibitor [see Drug Interactions (7.5) and Clinical Pharmacology (12.3)]
- Concurrent administration of propranolol [see Drug Interactions (7.1) and Clinical Pharmacology (12.3) ]
- Hypersensitivity to rizatriptan or any ingredients in RizaFilm (angioedema and anaphylaxis seen) [see Warnings and Precautions (5.6) ]

5 WARNINGS AND PRECAUTIONS

5.1 Myocardial Ischemia, Myocardial Infarction, and Prinzmetal's Angina

RizaFilm should not be given to patients with ischemic or vasospastic coronary artery disease. There have been rare reports of serious cardiac adverse reactions, including acute myocardial infarction, occurring within a few hours following administration of rizatriptan benzoate. Some of these reactions occurred in patients without known coronary artery disease (CAD). 5-HT1 agonists, including RizaFilm may cause coronary artery vasospasm (Prinzmetal's Angina), even in patients without a history of CAD.

Perform a cardiovascular evaluation in triptan-naïve patients who have multiple cardiovascular risk factors (e.g., increased age, diabetes, hypertension, smoking, obesity, strong family history of CAD) before receiving RizaFilm. If there is evidence of CAD or coronary artery vasospasm, RizaFilm is contraindicated. For patients with multiple cardiovascular risk factors who have a negative cardiovascular evaluation, consider administering the first RizaFilm dose in a medically supervised setting and performing an electrocardiogram (ECG) immediately following RizaFilm administration. For such patients, consider periodic cardiovascular evaluation in intermittent long-term users of RizaFilm.

5.2 Arrhythmias

Life-threatening disturbances of cardiac rhythm, including ventricular tachycardia and ventricular fibrillation leading to death, have been reported within a few hours following the administration of 5-HT1 agonists. Discontinue RizaFilm if these disturbances occur. RizaFilm is contraindicated in patients with Wolff-Parkinson-White syndrome or arrhythmias associated with other cardiac accessory conduction pathway disorder.

5.3 Chest, Throat, Neck, and/or Jaw Pain/Tightness/Pressure

Sensations of tightness, pain, pressure, and heaviness in the precordium, throat, neck, and jaw commonly occur after treatment with rizatriptan, the active moiety in RizaFilm, and are usually noncardiac in origin. However, perform a cardiac evaluation if these patients are at a high cardiac risk. The use of RizaFilm is contraindicated in patients with CAD and those with Prinzmetal's variant angina.

5.4 Cerebrovascular Events

Cerebral hemorrhage, subarachnoid hemorrhage, and stroke have occurred in patients treated with 5-HT1 agonists, and some have resulted in fatalities. In a number of cases, it appears possible that the cerebrovascular events were primary, the 5-HT1 agonist having been administered in the incorrect belief that the symptoms experienced were a consequence of migraine, when they were not. Also, patients with migraine may be at increased risk of certain cerebrovascular events (e.g., stroke, hemorrhage, transient ischemic attack). Discontinue RizaFilm if a cerebrovascular event occurs.

Before treating headaches in patients not previously diagnosed with migraine or in patients who present with atypical symptoms, exclude other potentially serious neurological conditions. RizaFilm is contraindicated in patients with a history of stroke or transient ischemic attack.

5.5 Other Vasospasm Reactions

5-HT1 agonists, including RizaFilm, may cause non-coronary vasospastic reactions, such as peripheral vascular ischemia, gastrointestinal vascular ischemia and infarction (presenting with abdominal pain and bloody diarrhea), splenic infarction, and Raynaud’s syndrome. In patients who experience symptoms or signs suggestive of non-coronary vasospasm reaction following the use of any 5-HT1 agonist, rule out the suspected vasospasm reaction before receiving additional RizaFilm doses.

Transient and permanent blindness and significant partial vision loss have been reported with the use of 5-HT1 agonists. Since visual disorders may be part of a migraine attack, a causal relationship between these events and the use of 5-HT1 agonists has not been clearly established.

5.6 Hypersensitivity Reactions

Hypersensitivity reactions, including angioedema and anaphylaxis, have occurred in patients receiving rizatriptan, the active moiety in RizaFilm. Such reactions can be life-threatening or fatal. In general, anaphylactic reactions to drugs are more likely to occur in individuals with a history of sensitivity to multiple allergens. RizaFilm is contraindicated in patients with a history of hypersensitivity reaction to rizatriptan.

5.7 Medication Overuse Headache

Overuse of acute migraine drugs (e.g., ergotamine, triptans, opioids, or a combination of drugs for 10 or more days per month) may lead to exacerbation of headache (medication overuse headache). Medication overuse headache may present as migraine-like daily headaches, or as a marked increase in the frequency of migraine attacks. Detoxification of patients, including withdrawal of the overused drugs, and treatment of withdrawal symptoms (which often includes a transient worsening of headache) may be necessary.

5.8 Serotonin Syndrome

Serotonin syndrome may occur with triptans, including RizaFilm, particularly during coadministration with selective serotonin reuptake inhibitors (SSRIs), serotonin norepinephrine reuptake inhibitors (SNRIs), tricyclic antidepressants (TCAs), and MAO inhibitors [see Drug Interactions (7.5) ]. Serotonin syndrome symptoms may include mental status changes (e.g., agitation, hallucinations, coma), autonomic instability (e.g., tachycardia, labile blood pressure, hyperthermia), neuromuscular aberrations (e.g., hyperreflexia, incoordination) and/or gastrointestinal symptoms (e.g., nausea, vomiting, diarrhea). The onset of symptoms can occur within minutes to hours of receiving a new or a greater dose of a serotonergic medication. RizaFilm treatment should be discontinued if serotonin syndrome is suspected [see Drug Interactions (7.4) and Patient Counseling Information (17) ].

5.9 Increase in Blood Pressure

Significant elevation in blood pressure, including hypertensive crisis with acute impairment of organ systems, has been reported on rare occasions in patients with and without a history of hypertension receiving 5-HT1 agonists, including rizatriptan benzoate. In healthy young adult male and female patients who received maximal doses of rizatriptan benzoate (10 mg every 2 hours for 3 doses), slight increases in blood pressure (approximately 2-3 mmHg) were observed. RizaFilm is contraindicated in patients with uncontrolled hypertension [see Contraindications (4) ].

6 ADVERSE REACTIONS

The following serious adverse reactions are discussed in more detail in other sections of the labeling:

- Myocardial Ischemia, Myocardial Infarction, and Prinzmetal's Angina [see Warnings and Precautions (5.1)].
- Arrhythmias [see Warnings and Precautions (5.2)].
- Chest and or Throat, Neck and/or Jaw Pain/Tightness/Pressure [see Warnings and Precautions (5.3)].
- Cerebrovascular Events [see Warnings and Precautions (5.4)].
- Other Vasospasm Reactions [see Warnings and Precautions (5.5)].
- Hypersensitivity Reactions [see Warnings and Precautions (5.6)]
- Medication Overuse Headache [see Warnings and Precautions (5.7)].
- Serotonin Syndrome [see Warnings and Precautions (5.8)].
- Increase in Blood Pressure [see Warnings and Precautions (5.9)].

6.1 Clinical Trials Experience

Because clinical studies are conducted under widely varying conditions, adverse reaction rates observed in the clinical studies of a drug cannot be directly compared to rates in the clinical studies of another drug and may not reflect the rates observed in practice.

The studies described below were conducted with rizatriptan benzoate tablets; adverse reactions with RizaFilm are expected to be similar to rizatriptan benzoate tablets.

Adults

Incidence in Controlled Clinical Trials

Adverse reactions to rizatriptan benzoate were assessed in controlled clinical trials that included over 3700 adult patients who received single or multiple doses of rizatriptan benzoate tablets. The most common adverse reactions during treatment with rizatriptan benzoate (≥5% in either treatment group and greater than placebo) were asthenia/fatigue, somnolence, pain/pressure sensation, dizziness, and nausea.

Table 1 lists the adverse reactions (incidence ≥2% and greater than placebo) after a single dose of rizatriptan benzoate in adults.

Table 1: Incidence (≥2% and Greater than Placebo) of Adverse Reactions After a Single Dose of Rizatriptan Benzoate Tablets or Placebo in Adults
 | % of Patients
Adverse Reactions |  | Rizatriptan; Benzoate; 10 mg; (N=1167) | Placebo; (N=627)
Atypical Sensations |  | 5 | 4
Paresthesia |  | 4 | <2
Pain and other Pressure Sensations |  | 9 | 3
Chest Pain:
tightness/pressure and/or heaviness |  | 3 | 1
Pain, location unspecified |  | 3 | <2
Neck/throat/jaw:
pain/tightness/pressure |  | 2 | 1
Regional Pain:
tightness/pressure and/or heaviness |  | 2 | 0
Digestive |  | 13 | 8
Nausea |  | 6 | 4
Dry Mouth |  | 3 | 1
Neurological |  | 20 | 11
Dizziness |  | 9 | 5
Somnolence |  | 8 | 4
Headache |  | 2 | <1
Other
Asthenia/fatigue |  | 7 | 2

The frequencies of adverse reactions in clinical trials did not increase when up to three doses were taken within 24 hours. Adverse reaction frequencies were also unchanged by concomitant use of drugs commonly taken for migraine prophylaxis, oral contraceptives, or analgesics. The incidences of adverse reactions were not affected by age or gender. There were insufficient data to assess the impact of race on the incidence of adverse reactions.

Other Events Observed in Association with the Administration of Rizatriptan Benzoate in Adults

In the following section, the frequencies of less commonly reported adverse events are presented that were not reported in other sections of the labeling. Because the reports include events observed in open studies, the role of rizatriptan benzoate in their causation cannot be reliably determined. Furthermore, variability associated with adverse event reporting, the terminology used to describe adverse events, limit the value of the quantitative frequency estimates provided. Event frequencies are calculated as the number of patients who used rizatriptan benzoate and reported an event divided by the total number of patients exposed to rizatriptan benzoate (N=3716). All reported events occurred at an incidence ≥1%, or are believed to be reasonably associated with the use of the drug. Events are further classified within body system categories and enumerated in order of decreasing frequency using the following definitions: frequent adverse events are those defined as those occurring in at least (>)1/100 patients; infrequent adverse experiences are those occurring in 1/100 to 1/1000 patients; and rare adverse experiences are those occurring in fewer than 1/1000 patients.

General: Infrequent was facial edema. Rare were syncope and edema/swelling.

Atypical Sensations: Frequent were warm sensations.

Cardiovascular: Frequent was palpitation. Infrequent were tachycardia, cold extremities, and bradycardia.

Digestive: Frequent were diarrhea and vomiting. Infrequent were dyspepsia, tongue edema and abdominal distention.

Musculoskeletal: Infrequent were muscle weakness, stiffness, myalgia and muscle cramp/spasm.

Neurological/Psychiatric: Frequent were hypoesthesia, euphoria and tremor. Infrequent were vertigo, insomnia, confusion/disorientation, gait abnormality, memory impairment, and agitation.

Respiratory: Frequent was dyspnea. Infrequent was pharyngeal edema.

Special Senses: Infrequent were blurred vision and tinnitus. Rare was eye swelling.

Skin and Skin Appendage: Frequent was flushing. Infrequent were sweating, pruritus, rash, and urticaria. Rare was erythema, hot flashes.

Pediatric Patients 12 to 17 Years of Age

Incidence in Controlled Clinical Trials in Pediatric Patients

Adverse reactions to rizatriptan benzoate orally disintegrating tablets were assessed in a controlled clinical trial for the acute treatment of migraine (Study 7) that included a total of 1382 pediatric patients (including those 12-17 years of age), of which 977 (72%) were administered at least one dose of study treatment (rizatriptan benzoate orally disintegrating tablets and/or placebo) [see Clinical Studies (14.2)]. The incidence of adverse reactions reported for pediatric patients in the acute clinical trial was similar in patients who received rizatriptan benzoate tablets to those who received placebo. The adverse reaction pattern in pediatric patients is expected to be similar to that in adults.

Other Events Observed in Association with the Administration of Rizatriptan Benzoate Orally Disintegrating Tablets in Pediatric Patients

In the following section, the frequencies of less commonly reported adverse events are presented. Because the reports include events observed in open studies, the role of rizatriptan benzoate orally disintegrating tablets in their causation cannot be reliably determined. Furthermore, variability associated with adverse event reporting, the terminology used to describe adverse events, limit the value of the quantitative frequency estimates provided.

Event frequencies are calculated as the number of pediatric patients (including those 12 to 17 years of age) who used rizatriptan benzoate orally disintegrating tablets and reported an event divided by the total number of patients exposed to rizatriptan benzoate orally disintegrating tablets (N=1068). All reported events occurred at an incidence ≥1%, or are believed to be reasonably associated with the use of the drug. Events are further classified within system organ class and enumerated in order of decreasing frequency using the following definitions: frequent adverse events are those occurring in (>)1/100 pediatric patients; infrequent adverse experiences are those occurring in 1/100 to 1/1000 pediatric patients, and rare adverse experiences are those occurring in fewer than 1/1000 patients.

General: Frequent was fatigue.

Ear and labyrinth disorders: Infrequent was hypoacusis.

Gastrointestinal disorders: Frequent was abdominal discomfort.

Nervous system disorders: Infrequent were coordination abnormal, disturbance in attention, and presyncope.

Psychiatric disorders: Infrequent was hallucination.

6.2 Postmarketing Experience

The following adverse reactions have been identified during postapproval use of rizatriptan. Because these reactions are reported voluntarily from a population of uncertain size, it is not always possible to reliably estimate their frequency or establish a causal relationship to drug exposure.

Neurological/Psychiatric: Seizure.

General: Allergic conditions including anaphylaxis/anaphylactoid reaction, angioedema, wheezing, and toxic epidermal necrolysis [see Contraindications (4)].

Special Senses: Dysgeusia.

7 DRUG INTERACTIONS

7.1 Propranolol

Because propranolol increases the exposure of rizatriptan and dosage adjustment is not possible with RizaFilm, concomitant use of RizaFilm with propranolol is contraindicated [see Contraindications (4) and Clinical Pharmacology (12.3)] .

7.2 Ergot-Containing Drugs

Ergot-containing drugs have been reported to cause prolonged vasospastic reactions. Because these effects may be additive, use of ergotamine-containing or ergot-type medications (like dihydroergotamine or methysergide) and RizaFilm within 24 hours is contraindicated [ see Contraindications (4)].

7.3 Other 5-HT1 Agonists

Because their vasospastic effects may be additive, co-administration of RizaFilm and other 5-HT1 agonists within 24 hours of each other is contraindicated [ see Contraindications (4) ].

7.4 SSRIs/SNRIs and Serotonin Syndrome

Cases of serotonin syndrome have been reported during co-administration of triptans and selective serotonin reuptake inhibitors (SSRIs) or serotonin norepinephrine reuptake inhibitors (SNRIs) [see Warnings and Precautions (5.7)] .

7.5 Monoamine Oxidase Inhibitors

Because of an increase in the systemic exposure of rizatriptan and its metabolite, RizaFilm is contraindicated in patients taking MAO-A inhibitors and non-selective MAO inhibitors [see Contraindications (4) and Clinical Pharmacology (12.3)] .

8 USE IN SPECIFIC POPULATIONS

8.1 Pregnancy

Risk Summary

Available human data on the use of rizatriptan in pregnant women are not sufficient to draw conclusions about drug-associated risk for major birth defects and miscarriage.

In animal studies, developmental toxicity was observed following oral administration of rizatriptan during pregnancy (decreased fetal body weight in rats) or throughout pregnancy and lactation (increased mortality, decreased body weight, and neurobehavioral impairment in rat offspring) at maternal plasma exposures greater than that expected at therapeutic doses in humans [see Animal Data].

In the U.S. general population, the estimated background risk of major birth defects and miscarriage in clinically recognized pregnancies is 2% to 4% and 15% to 20%, respectively. The reported rate of major birth defects among deliveries to women with migraine range from 2.2% to 2.9% and the reported rate of miscarriage was 17%, which are similar to rates reported in women without migraine.

Clinical Considerations

Disease-Associated Maternal and/or Embryo/Fetal Risk
In women with migraine, there is an increased risk of adverse perinatal outcomes in the mother, including pre-eclampsia and gestational hypertension.

Data

Human Data

The Pregnancy Registry for rizatriptan did not identify any pattern of congenital anomalies or other adverse birth outcomes over the period of 1998 to 2018. However, the lack of identification of any pattern should be viewed with caution, as the number of prospective reports with outcome information was low and did not provide sufficient power to detect an increased risk of individual birth defects associated with the use of rizatriptan. Additionally, there was significant loss to follow-up in the prospective pregnancy reports, further complicating this assessment of an association between rizatriptan and any pattern of congenital anomalies or other adverse birth outcomes.

In a study using data from the Swedish Medical Birth Register, live births to women who reported using triptans or ergots during pregnancy were compared with those of women who did not. Of the 157 births with first-trimester exposure to rizatriptan, 7 infants were born with malformations (relative risk 1.01 [95% CI: 0.40 to 2.08]). A study using linked data from the Medical Birth Registry of Norway to the Norwegian Prescription Database compared pregnancy outcomes in women who redeemed prescriptions for triptans during pregnancy, as well as a migraine disease comparison group who redeemed prescriptions for triptans before pregnancy only, compared with a population control group. Of the 310 women who redeemed prescriptions for rizatriptan during the first trimester, 10 had infants with major congenital malformations (OR 1.03 [95% CI: 0.55 to 1.93]), while for the 271 women who redeemed prescriptions for rizatriptan before but not during pregnancy, 12 had infants with major congenital malformations (OR 1.48 [95% CI: 0.83 to 2.64]), each compared with the population comparison group.

Animal Data

When rizatriptan (0, 2, 10, or 100 mg/kg/day) was administered orally to pregnant rats throughout organogenesis, a decrease in fetal body weight was observed at the highest doses tested. At the mid-dose (10 mg/kg/day), which was a no-effect dose for adverse effects on embryofetal development, plasma exposure (AUC) was approximately 15 times that in humans at the maximum recommended human dose (MRHD) of 30 mg/day. When rizatriptan (0, 5, 10, or 50 mg/kg/day) was administered orally to pregnant rabbits throughout organogenesis, no adverse fetal effects were observed. Plasma exposure (AUC) at the highest dose tested was 115 times that in humans at the MRHD. Placental transfer of the drug to the fetus was demonstrated in both species.

Oral administration of rizatriptan (0, 2, 10, or 100 mg/kg/day) to female rats before and during mating and continuing throughout gestation and lactation resulted in reduced body weight in offspring from birth and throughout lactation at all but the lowest dose tested (2 mg/kg/day). Plasma exposure (AUC) at the no-effect dose (2 mg/kg/day) for adverse effects on postnatal development was similar to that in humans at the MRHD.

Oral administration of rizatriptan (0, 5, 100, or 250 mg/kg/day) throughout organogenesis and lactation resulted in neonatal mortality, reduced body weight (which persisted into adulthood), and impaired neurobehavioral function in offspring at all but the lowest dose tested. Plasma exposure (AUC) at the no-effect dose for adverse effects on postnatal development (5 mg/kg/day) was approximately 8 times that in humans at the MRHD.

8.2 Lactation

Risk Summary

There are no data on the presence of rizatriptan or any active metabolites in human milk or on the effects of rizatriptan on the breastfed infant, or milk production.

Rizatriptan was excreted in rat milk, with levels in milk approximately 6 times those in maternal plasma.

The developmental and health benefits of breastfeeding should be considered along with the mother’s clinical need for RizaFilm and any potential adverse effects on the breastfed infant from RizaFilm or the underlying maternal condition.

Data

Following oral administration of rizatriptan to lactating rats at a dose of 100 mg/kg/day, the drug concentrations of rizatriptan in milk samples exceeded maternal plasma drug concentrations by approximately 6-fold.

8.4 Pediatric Use

The safety and effectiveness of RizaFilm for the acute treatment of migraine have been established in pediatric patients 12 years of age and older weighing 40 kg or more based on an adequate and well-controlled study with rizatriptan benzoate tablets [see Clinical Studies (14.2)].

The incidence of adverse reactions reported for pediatric patients in the acute clinical trial was similar in patients who received rizatriptan benzoate tablets to those who received placebo. The adverse reaction pattern in pediatric patients is expected to be similar to that in adults.

Safety and effectiveness of RizaFilm in pediatric patients under 12 years of age and weighing less than 40 kg have not been established.

8.5 Geriatric Use

Clinical studies of rizatriptan benzoate did not include sufficient numbers of subjects aged 65 and over to determine whether they respond differently from younger subjects. Other reported clinical experience has not identified differences in responses between the elderly and younger patients.

The pharmacokinetics of rizatriptan were similar in elderly (aged ≥65 years) and younger adults (n=17) [see Clinical Pharmacology (12.3) ].

Geriatric patients who have cardiovascular risk factors (e.g., diabetes, hypertension, smoking, obesity, strong family history of coronary artery disease) should have a cardiovascular evaluation before receiving RizaFilm [see Warnings and Precautions (5.1) ].

10 OVERDOSAGE

No overdoses of rizatriptan benzoate were reported during clinical trials in adults.

Some adult patients who received 40 mg of rizatriptan benzoate either in a single dose or as two doses with a 2-hour interdose interval had dizziness and somnolence.

In a clinical pharmacology study in which 12 adult subjects received rizatriptan benzoate, at total cumulative doses of 80 mg (given within four hours), two of the subjects experienced syncope, dizziness, bradycardia including third degree AV block, vomiting, and/or incontinence.

In the long-term, open label study, involving 606 treated pediatric migraineurs 12 to 17 years of age (of which 432 were treated for at least 12 months), 151 patients (25%) took two 10-mg doses of Rizatriptan Benzoate Orally Disintegrating Tablets within a 24-hour period. Adverse reactions for 3 of these patients included abdominal discomfort, fatigue, and dyspnea.

In addition, based on the pharmacology of rizatriptan benzoate, hypertension or myocardial ischemia could occur after overdosage. Gastrointestinal decontamination, (i.e., gastric lavage followed by activated charcoal) should be considered in patients suspected of an overdose with RizaFilm. Clinical and electrocardiographic monitoring should be continued for at least 12 hours, even if clinical symptoms are not observed.

The effects of hemo- or peritoneal dialysis on serum concentrations of rizatriptan are unknown.

11 DESCRIPTION

RizaFilm contains rizatriptan benzoate, a selective 5-hydroxytryptamine1B/1D (5-HT1B/1D) receptor agonist.

Rizatriptan benzoate is described chemically as: N,N-dimethyl-5-(1 H-1,2,4-triazol-1-ylmethyl)-1 H-indole-3-ethanamine monobenzoate and its structural formula is:

Its empirical formula is C15H19N5•C7H6O2, representing a molecular weight of the free base of 269.4. Rizatriptan benzoate is a white to off-white, crystalline solid that is soluble in water at about 42 mg per mL (expressed as free base) at 25°C.

RizaFilm oral film is available for oral administration in a 10 mg strength (equivalent to 14.53 mg rizatriptan benzoate). Each oral film contains the following inactive ingredients: ammonium glycyrrhizate, butylated hydroxytoluene, copovidone, cupric chloride, ethylcellulose, FD&C Blue No. 1, hydroxypropyl cellulose, isopropyl alcohol, levomenthol, methyl ethyl ketone, sodium acetate, sucralose, titanium dioxide, and triacetin.

12 CLINICAL PHARMACOLOGY

12.1 Mechanism of Action

Rizatriptan binds with high affinity to human cloned 5-HT1B/1D receptors. RizaFilm presumably exerts its therapeutic effects in the treatment of migraine headache by binding to 5-HT1B/1D receptors located on intracranial blood vessels and sensory nerves of the trigeminal system.

12.2 Pharmacodynamics

Blood Pressure: Significant elevation in blood pressure, including hypertensive crisis, has been reported in patients treated with rizatriptan, with and without a history of hypertension [see Warnings and Precautions (5.9) ].

12.3 Pharmacokinetics

Absorption

Rizatriptan is completely absorbed following oral administration. The mean oral absolute bioavailability of the rizatriptan benzoate tablet is about 45% and mean peak plasma concentrations (Cmax) are reached in approximately 1-1.5 hours (Tmax). The presence of a migraine headache did not appear to affect the absorption or pharmacokinetics of rizatriptan. Food has no significant effect on the bioavailability of rizatriptan but delays the time to reach peak concentration by an hour. In clinical trials, rizatriptan benzoate tablets were administered without regard to food.

The bioavailability and Cmax of rizatriptan were similar following administration of rizatriptan benzoate tablets and rizatriptan benzoate orally disintegrating tablets, but the rate of absorption is somewhat slower with the orally disintegrating tablets, with Tmax delayed by up to 0.7 hour. AUC of rizatriptan is approximately 30% higher in females than in males. No accumulation occurred on multiple dosing.

Following a single dose of 10mg RizaFilm, the mean Cmax and AUCinf of rizatriptan were 23.79 (± 8.36) ng/mL and 84.54 (± 18.65) ng·hr/mL, respectively; the maximum peak plasma concentrations were achieved in 1.4 hours.

Distribution

The mean volume of distribution is approximately 140 liters in male subjects and 110 liters in female subjects. Rizatriptan is minimally bound (14%) to plasma proteins.

Metabolism

The primary route of rizatriptan metabolism is via oxidative deamination by monoamine oxidase-A (MAO-A) to the indole acetic acid metabolite, which is not active at the 5-HT1B/1D receptor. N-monodesmethyl-rizatriptan, a metabolite with activity similar to that of parent compound at the 5-HT1B/1D receptor, is formed to a minor degree. Plasma concentrations of N-monodesmethyl-rizatriptan are approximately 14% of those of parent compound, and it is eliminated at a similar rate. Other minor metabolites, the N-oxide, the 6-hydroxy compound, and the sulfate conjugate of the 6-hydroxy metabolite are not active at the 5-HT1B/1D receptor.

Elimination

The total radioactivity of the administered dose recovered over 120 hours in urine and feces was 82% and 12%, respectively, following a single 10-mg oral administration of^14C-rizatriptan. Following oral administration of^14C-rizatriptan, rizatriptan accounted for about 17% of circulating plasma radioactivity. Approximately 14% of an oral dose is excreted in urine as unchanged rizatriptan while 51% is excreted as indole acetic acid metabolite, indicating substantial first-pass metabolism.

Following administration of RizaFilm, the mean plasma half-life of rizatriptan is 2 hours.

Cytochrome P450 Isoforms

Rizatriptan is not an inhibitor of the activities of human liver cytochrome P450 isoforms 3A4/5, 1A2, 2C9, 2C19, or 2E1; rizatriptan is a competitive inhibitor (Ki =1400 nM) of cytochrome P450 2D6, but only at high, clinically irrelevant concentrations.

Specific Populations

Geriatric: Rizatriptan pharmacokinetics in healthy elderly non-migraineur volunteers (age 65-77 years) were similar to those in younger non-migraineur volunteers (age 18-45 years).

Pediatric: The pharmacokinetics of rizatriptan was determined in pediatric migraineurs 12 to 17 years of age. Exposures following single-dose administration of 10 mg rizatriptan benzoate orally disintegrating tablets to pediatric patients weighing ≥40 kg (88 lb) were similar to those observed following single-dose administration of 10 mg rizatriptan benzoate orally disintegrating tablets to adults.

Gender: The mean AUC0-∞ and Cmax of rizatriptan (10 mg orally) were about 30% and 11% higher in females as compared to males, respectively, while Tmax occurred at approximately the same time.

Patients with Hepatic Impairment: Following oral administration in patients with hepatic impairment caused by mild to moderate alcoholic cirrhosis of the liver, plasma concentrations of rizatriptan were similar in patients with mild hepatic insufficiency compared to a control group of subjects with normal hepatic function; plasma concentrations of rizatriptan were approximately 30% greater in patients with moderate hepatic insufficiency.

Patients with Renal Impairment: In patients with renal impairment (creatinine clearance 10-60 mL/min/1.73 m^2), the AUC0-∞ of rizatriptan was not significantly different from that in subjects with normal renal function. In hemodialysis patients, (creatinine clearance <2 mL/min/1.73 m2), however, the AUC for rizatriptan was approximately 44% greater than that in patients with normal renal function.

Race: Pharmacokinetic data revealed no significant differences between African American and Caucasian subjects.

Drug Interactions

Monoamine Oxidase Inhibitors: In a drug interaction study, when rizatriptan benzoate 10 mg tablets were administered to subjects (n=12) receiving concomitant therapy with the selective, reversible MAO-A inhibitor, moclobemide 150 mg three times a day, there were mean increases in rizatriptan AUC and Cmax of 119% and 41%, respectively; and the AUC of the active N-monodesmethyl metabolite of rizatriptan was increased more than 400%. The interaction would be expected to be greater with irreversible MAO inhibitors [see Contraindications (4) and Drug Interactions (7.5)]. No pharmacokinetic interaction is anticipated in patients receiving selective MAO-B inhibitors.

Propranolol: In a study of concurrent administration of propranolol 240 mg/day and a single dose of rizatriptan 10 mg in healthy adult subjects (n=11), mean plasma AUC for rizatriptan was increased by 70%, and a four-fold increase was observed in one subject [see Contraindications (4) and Drug Interactions (7.1) ]. The AUC of the active N-monodesmethyl metabolite of rizatriptan was not affected by propranolol.

Nadolol/Metoprolol: In a drug interactions study, effects of multiple doses of nadolol 80 mg or metoprolol 100 mg every 12 hours on the pharmacokinetics of a single dose of 10 mg rizatriptan were evaluated in healthy subjects (n=12). No pharmacokinetic interactions were observed.

Paroxetine: In a study of the interaction between the selective serotonin reuptake inhibitor (SSRI) paroxetine 20 mg/day for two weeks and a single dose of rizatriptan benzoate tablet 10 mg in healthy subjects (n=12), neither the plasma concentrations of rizatriptan nor its safety profile were affected by paroxetine [see Warnings and Precautions (5.7) , Drug Interactions (7.4) , and Patient Counseling Information (17) ].

Oral Contraceptives: In a study of concurrent administration of an oral contraceptive during 6 days of administration of rizatriptan (10-30 mg/day) in healthy female volunteers (n=18), rizatriptan did not affect plasma concentrations of ethinyl estradiol or norethindrone.

13 NONCLINICAL TOXICOLOGY

13.1 Carcinogenesis, Mutagenesis, Impairment of Fertility

Carcinogenesis

Oral carcinogenicity studies were conducted in mice (100 weeks) and rats (106 weeks) at doses of up to 125 mg/kg/day. Plasma exposures (AUC) at the highest dose tested were approximately 150 (mice) and 240 times (rats) that in humans at the maximum recommended daily dose (MRDD) of 30 mg/day. There was no evidence of an increase in tumor incidence related to rizatriptan in either species.

Mutagenesis

Rizatriptan was neither mutagenic nor clastogenic in a battery of in vitro and in vivo genetic toxicity studies, including the microbial mutagenesis (Ames) assay, in vitro mammalian cell mutagenesis and chromosomal aberration assays, and the in vivo chromosomal aberration assay in mouse.

Impairment of Fertility

In a fertility study in rats, altered estrus cyclicity and delays in time to mating were observed in females treated orally with 100 mg/kg/day rizatriptan. The no-effect dose was 10 mg/kg/day (approximately 15 times the human exposure at the MRDD). There were no other fertility-related effects in the female rats. There was no impairment of fertility or reproductive performance in male rats treated with up to 250 mg/kg/day (approximately 550 times the human exposure at the MRDD).

14 CLINICAL STUDIES

The studies described below establishing effectiveness for the acute treatment of migraine with or without aura were conducted with rizatriptan benzoate tablets. The efficacy of RizaFilm is based on a relative bioavailability study comparing RizaFilm 10 mg oral film to rizatriptan benzoate 10 mg tablets [see Clinical Pharmacology (12.3) ].

14.1 Adults

The efficacy of rizatriptan benzoate tablets was established in four multicenter, randomized, placebo-controlled trials. Patients enrolled in these studies were primarily female (84%) and Caucasian (88%), with a mean age of 40 years (range of 18 to 71). Patients were instructed to treat a moderate to severe headache. Headache response, defined as a reduction of moderate or severe headache pain to no or mild headache pain, was assessed for up to 2 hours (Study 1) or up to 4 hours after dosing (Studies 2, 3, and 4). Associated symptoms of nausea, photophobia, and phonophobia and maintenance of response up to 24 hours post-dose were evaluated. A second dose of rizatriptan benzoate tablets was allowed 2 to 24 hours after dosing for treatment of recurrent headache in Studies 1 and 2. Additional analgesics and/or antiemetics were allowed 2 hours after initial treatment for rescue in all four studies.

In all studies, the percentage of patients achieving headache response 2 hours after treatment was significantly greater in patients who received rizatriptan 10 mg compared to those who received placebo. Doses greater than 10 mg were associated with an increased incidence of adverse effects. The results from the four controlled studies are summarized in Table 2.

Table 2: Response Rates 2 Hours Following Treatment of Initial Headaches in Studies 1, 2, 3, and 4
Study | Placebo | Rizatriptan tablets 10mg
1 | 35% (n=304) | 71% *(n=456)
2** | 37% (n=82) | 77% *(n=320)
3 | 23% (n=80) | -
4 | 40% (n=159) | 67%*(n=385)
*p-value <0.05 in comparison with placebo.
**Results for initial headache only.

Comparisons of drug performance based upon results obtained in different clinical trials may not be reliable. Because studies are conducted at different times, with different samples of patients, by different investigators, employing different criteria and/or different interpretations of the same criteria, under different conditions (dose, dosing regimen, etc.), quantitative estimates of treatment response and the timing of response may be expected to vary considerably from study to study.

The estimated probability of achieving an initial headache response within 2 hours following treatment in pooled Studies 1, 2, 3, and 4 is depicted in Figure 1.

Figure 1: Estimated Probability of Achieving an Initial Headache Response by 2 Hours in Pooled Studies 1, 2, 3, and 4*

* Figure 1 shows the Kaplan-Meier plot of the probability over time of obtaining headache response (no or mild pain) following treatment with rizatriptan benzoate tablets or placebo. The averages displayed are based on pooled data from 4 placebo-controlled, outpatient trials providing evidence of efficacy (Studies 1, 2, 3, and 4). Patients taking additional treatment or not achieving headache response before 2 hours were censored at 2 hours.

For patients with migraine-associated photophobia, phonophobia, and nausea at baseline, there was a decreased incidence of these symptoms following administration of rizatriptan benzoate tablets compared to placebo.

Two to 24 hours following the initial dose of study treatment, patients were allowed to use additional treatment for pain response in the form of a second dose of study treatment or other medication. The estimated probability of patients taking a second dose or other medication for migraine over the 24 hours following the initial dose of study treatment is summarized in Figure 2.

Figure 2: Estimated Probability of Patients Taking a Second Dose of Rizatriptan Benzoate Tablets or Other Medication for Migraines Over the 24 Hours Following the Initial Dose of Study Treatment in Pooled Studies 1, 2, 3, and 4*

* This Kaplan-Meier plot is based on data obtained in 4 placebo-controlled outpatient clinical trials (Studies 1, 2, 3, and 4). Patients not using additional treatments were censored at 24 hours. The plot includes both patients who had headache response at 2 hours and those who had no response to the initial dose. Remedication was not allowed within 2 hours post-dose.

Efficacy was unaffected by the presence of aura; by the gender, or age of the patient; or by concomitant use of common migraine prophylactic drugs (e.g., beta-blockers, calcium channel blockers, tricyclic antidepressants) or oral contraceptives. In two additional similar studies, efficacy was unaffected by relationship to menses. There were insufficient data to assess the impact of race on efficacy.

Rizatriptan Benzoate Orally Disintegrating Tablets

The efficacy of rizatriptan benzoate orally disintegrating tablets was established in two multicenter, randomized, placebo-controlled trials that were similar in design to the trials of rizatriptan benzoate tablets (Studies 5 and 6). Patients were instructed to treat a moderate to severe headache. Patients treated in these studies were primarily female (88%) and Caucasian (95%), with a mean age of 42 years (range 18-72).

In both studies, the percentage of patients achieving headache response 2 hours after treatment was significantly greater in patients who received rizatriptan benzoate orally disintegrating tablets 10 mg compared to those who received placebo. The results from Studies 5 and 6 are summarized in Table 3.

Table 3: Response Rates 2 Hours Following Treatment of Initial Headache in Studies 5 and 6
Study | Placebo | Rizatriptan orally disintegrating tablets 10mg
5 | 47% (n=98) | 66%*(n=113)
6 | 28% (n=180) | 74%*(n=186)
*p-value <0.01 in comparison with placebo

The estimated probability of achieving an initial headache response by 2 hours following treatment with rizatriptan benzoate orally disintegrating tablets in pooled Studies 5 and 6 is depicted in Figure 3.

Figure 3: Estimated Probability of Achieving an Initial Headache Response with Rizatriptan Benzoate Orally Disintegrating Tablets by 2 Hours in pooled Studies 5 and 6*

* Figure 3 shows the Kaplan-Meier plot of the probability over time of obtaining headache response (no or mild pain) following treatment with rizatriptan benzoate orally disintegrating tablets or placebo. The averages displayed are based on pooled data from 2 placebo-controlled, outpatient trials providing evidence of efficacy (Studies 5 and 6). Patients taking additional treatment or not achieving headache response before 2 hours were censored at 2 hours.

For patients with migraine-associated photophobia and phonophobia at baseline, there was a decreased incidence of these symptoms following administration of rizatriptan benzoate orally disintegrating tablets as compared to placebo.

Two to 24 hours following the initial dose of study treatment, patients were allowed to use additional treatment for pain response in the form of a second dose of study treatment or other medication. The estimated probability of patients taking a second dose or other medication for migraine over the 24 hours following the initial dose of study treatment is summarized in Figure 4.

Figure 4: Estimated Probability of Patients Taking a Second Dose of Rizatriptan Benzoate Orally Disintegrating Tablets or Other Medication for Migraines Over the 24 Hours Following the Initial Dose of Study Treatment in Pooled Studies 5 and 6*

* This Kaplan-Meier plot is based on data obtained in 2 placebo-controlled outpatient clinical trials (Studies 5 and 6). Patients not using additional treatments were censored at 24 hours. The plot includes both patients who had headache response at 2 hours and those who had no response to the initial dose. Remedication was not allowed within 2 hours post-dose.

14.2 Pediatric Patients 12 to 17 Years of Age

The efficacy of rizatriptan benzoate orally disintegrating tablets in pediatric patients 12 to 17 years of age was evaluated in a multicenter, randomized, double-blind, placebo-controlled, parallel-group clinical trial (Study 7). Patients had to have at least a 6-month history of migraine attacks (with or without aura) usually lasting 3 hours or more (when untreated). The patient population was historically non-responsive to NSAIDs and acetaminophen therapy.

Patients were instructed to treat a single migraine attack with headache pain of moderate to severe intensity. The treatment phase of the study had two stages. Stage 1 was used to identify placebo non-responders, who then entered into Stage 2, in which patients were randomized to rizatriptan benzoate orally disintegrating tablets or placebo. Using a weight-based dosing strategy, patients 12 to 17 years of age and weighing greater than or equal to 40 kg received rizatriptan benzoate orally disintegrating tablets 10 mg or placebo.

Of the total pediatric population in Study 7, including those weighing 40 kg or more, sixty-one percent of the patients were Caucasian, and fifty-six percent of the patients were female. The percentage of patients achieving the primary efficacy endpoint of no headache pain at 2 hours after treatment was significantly greater in patients who received rizatriptan benzoate orally disintegrating tablets, compared with those who received placebo (33% vs. 24%). Study 7 results are summarized in Table 4.

Table 4: Response Rates 2 Hours Following Treatment of Initial Headache in Pediatric Patients (including 12 to 17 Years of Age) in Study 7
Endpoint | Placebo | Rizatriptan orally disintegrating tablets | p-Value
No headache pain at 2 hours post-dose | 24% (n/m = 94/388) | 33% (n/m = 126/382) | 0.01
n = Numbr of evaluable patients with no headache pain at 2 hours post dose.m = Number of evaluable patients in population.

The observed percentage of pediatric patients achieving no headache pain within 2 hours following initial treatment with rizatriptan benzoate orally disintegrating tablets is shown in Figure 5.

Figure 5: Observed Percentage of Patients Reporting No Headache Pain by 2 Hours Post Dose in Study 7

The prevalence of the exploratory endpoints of absence of migraine-associated symptoms (nausea, photophobia, and phonophobia) at 2 hours after taking the dose was not statistically significantly different between patients who received rizatriptan benzoate orally disintegrating tablets and those who received placebo.

16 HOW SUPPLIED/STORAGE AND HANDLING

16.1 How Supplied

RizaFilm oral film, 10 mg is a white flexible rectangular strip of 2.2 cm × 2.75 cm with an imprint "RIZA10" in edible blue ink on one side. Each oral film is individually packaged in an aluminum laminate pouch. It is supplied as follows:

NDC 35781-0600-8. 1 carton of 18 individually packaged films.

16.2 Storage and Handling

Store RizaFilm at room temperature, 20°C to 25°C (68°F to 77°F); excursions permitted from 15°C to 30°C (59°F to 86°F) [see USP Controlled Room Temperature]. Keep product in pouch until ready to use.

17 PATIENT COUNSELING INFORMATION

Advise the patient to read the FDA-approved patient labeling (Patient Information).

Administration Instructions

Advise patients to fold the pouch on the dotted line and tear open at the notch. Inform patients that administration with liquids is not necessary. Direct patients to place RizaFilm oral film on the tongue, where it will disintegrate and be swallowed with saliva [see Dosage and Administration (2.3)].

Risk of Myocardial Ischemia and/or Infarction, Prinzmetal's Angina, Other Vasospasm-Related Events, and Cerebrovascular Events

Inform patients that RizaFilm may cause serious cardiovascular side effects such as myocardial infarction or stroke. Although serious cardiovascular events can occur without warning symptoms, patients should be alert for the signs and symptoms of chest pain, shortness of breath, weakness, slurring of speech, and should ask for medical advice when observing any indicative signs or symptoms. Patients should be apprised of the importance of this follow-up [see Warnings and Precautions (5.1, 5.2, 5.4, 5.5) ].

Serotonin Syndrome

Patients should be cautioned about the risk of serotonin syndrome with the use of RizaFilm or other triptans, particularly during combined use with selective serotonin reuptake inhibitors (SSRIs) or serotonin norepinephrine reuptake inhibitors (SNRIs) [ see Warnings and Precautions (5.7), Drug Interactions (7.4), and Clinical Pharmacology (12.3) ].

Pregnancy

Advise patients to notify their healthcare provider if they become pregnant during treatment or plan to become pregnant [ see Use in Specific Populations (8.1) ].

Lactation

Advise patients to notify their healthcare provider if they are breastfeeding or plan to breastfeed [see Use in Specific Populations (8.2)].

Ability To Perform Complex Tasks

Since migraines or treatment with RizaFilm may cause somnolence and dizziness, instruct patients to evaluate their ability to perform complex tasks during migraine attacks and after administration of RizaFilm.

Hypersensitivity Reactions

Inform patients that hypersensitivity reactions, including angioedema and anaphylaxis, have occurred in patients receiving rizatriptan. Inform patients that such reactions can be life threatening or fatal and to seek immediate medical attention if they have anaphylactic symptoms [see Warnings and Precautions (5.6) ].

Medication Overuse Headache

Inform patients that use of acute migraine drugs for 10 or more days per month may lead to an exacerbation of headache and encourage patients to record headache frequency and drug use (e.g., by keeping a headache diary) [ see Warnings and Precautions (5.7) ].

RizaFilm® is manufactured by:
IntelGenx Corp.

Saint-Laurent, Quebec H4S 1Y2 Canada

RizaFilm® is manufactured for:
Gensco Pharma

Doral, FL 33122

Revised: 12/2023

Patient Information

RizaFilm™ (ri’ zah film)

rizatriptan

oral film

What is RIZAFILM?

- RizaFilm is a prescription medicine that belongs to a class of medicines called Triptans. RizaFilm is available as oral films.
- RizaFilm is used to treat migraine attacks with or without aura in adults and in children 12 to 17 years of age who weigh 40 kg or more.
- RizaFilm is not to be used to prevent migraine attacks.
- It is not known if RizaFilm is safe and effective for the treatment of cluster headaches.
- It is not known if RizaFilm is safe and effective in children under 12 years of age and who weigh less than 40 kg.

Do not take RizaFilm if you:

- have or have had heart problems.
- have or have had a stroke or a transient ischemic attack (TIA).
- have or have had blood vessel problems including ischemic bowel disease, or narrowing of blood vessels in your legs, arms, and stomach, or kidney (peripheral vascular disease)
- have uncontrolled high blood pressure.
- have taken other Triptan medicines in the last 24 hours.
- have taken ergot-containing medicines in the last 24 hours.
- have hemiplegic or basilar migraines.
- take a monoamine oxidase (MAO) inhibitor or have taken a MAO inhibitor within the last 2 weeks.
- take propranolol.
- are allergic to rizatriptan or any of the ingredients in RizaFilm. See the end of this leaflet for a complete list of ingredients in RizaFilm.

Talk to your doctor before taking this medicine if you have any of the conditions listed above or if you are not sure if you take any of these medicines.

Before you take RizaFilm, tell your doctor about all of your medical conditions, including if you:

- have or have had heart problems, high blood pressure, chest pain, or shortness of breath.
- have any risk factors for heart problems or blood vessel problems such as:

o high blood pressure.
o high cholesterol.
o smoking.
o obesity.
o diabetes.
o family history of heart problems.
o you are post-menopausal.

- have kidney or liver problems.
- are pregnant or plan to become pregnant. It is not known if RizaFilm will harm your unborn baby. If you become pregnant while taking RizaFilm, talk to your healthcare provider.
- are breastfeeding or plan to breastfeed. It is not known if RizaFilm passes into your breast milk. Talk to your healthcare provider about the best way to feed your baby if you take RizaFilm.

Tell your doctor about all the medicines you take, including prescription and over-the-counter medicines, vitamins, and herbal supplements.

RizaFilm and other medicines may affect each other causing side effects. RizaFilm may affect the way other medicines work, and other medicines may affect how RizaFilm works.

Especially tell your doctor if you take:

- propranolol containing medicines such as Inderal, Inderal LA, or Innopran XL
- medicines used to treat mood disorders, including selective serotonin reuptake inhibitors (SSRIs) or serotonin norepinephrine reuptake inhibitors (SNRIs).

Ask your doctor or pharmacist for a list of these medicines, if you are not sure.

Know the medicines you take. Keep a list of them to show your doctor and pharmacist when you get a new medicine.

How should I take RizaFilm?

- Take RizaFilm exactly as your doctor tells you to take it.
- Your doctor will tell you how much RizaFilm to take and when to take it.
- To take RizaFilm:
  o Leave RizaFilm oral film in the aluminum pouch it comes in until you are ready to take it.
  o When you are ready to take it:
  o Remove the oral film from the aluminum pouch by folding the pouch on the dotted line and tearing it open at the tear notch.
  o Place the oral film on the tongue.
  o The oral film will disintegrate in about 2 minutes and can be swallowed with saliva. No liquid is required to take the oral film.
- If your headache comes back after your first RizaFilm dose:
  o For adults: a second dose may be taken at least 2 hours after the first dose. Do not take more than 30 mg of RizaFilm in a 24-hour period (for example, do not take more than 3 10-mg oral films in a 24-hour period).
  o For children 12 to 17 years of age: It is not known if taking more than 1 dose of RizaFilm in 24 hours is safe and effective. Talk to your doctor about what to do if your headache does not go away or comes back.
- If you take too much RizaFilm, call your doctor or go to the nearest hospital emergency room right away.

What should I avoid while taking RizaFilm?

RizaFilm may cause dizziness, weakness, or fainting. If you have these symptoms, do not drive a car, use machinery, or do anything that needs you to be alert.

What are the possible side effects of RizaFilm?

RizaFilm may cause serious side effects. Call your doctor or go to the nearest hospital emergency room right away if you think you are having any of the serious side effects of RizaFilm including:

- heart attack and other heart problems. Symptoms of a heart attack may include:
  o chest discomfort in the center of your chest that lasts for more than a few minutes or that goes away and comes back
  o chest discomfort that feels like uncomfortable pressure, squeezing, fullness or pain
  o pain or discomfort in your arms, back, neck, jaw or stomach
  o shortness of breath with or without chest discomfort
  o breaking out in a cold sweat
  o nausea or vomiting
  o feeling lightheaded

- stroke. Symptoms of a stroke may include the following sudden symptoms:
  o numbness or weakness in your face, arm or leg, especially on one side of your body
  o confusion, problems speaking or understanding
  o problems seeing in 1 or both of your eyes
  o problems walking, dizziness, loss of balance or coordination
  o severe headache with no known cause

- blood vessel problems. Symptoms of blood vessel problems may include:
  o stomach pain
  o bloody diarrhea
  o vision problems
  o coldness and numbness of hands and feet

- allergic reactions. Allergic reactions that can lead to death have happened in people who take rizatriptan, an ingredient in RizaFilm. Symptoms of an allergic reaction may include:
  o swelling of your face, eyes, lips, mouth, or tongue
  o trouble breathing
  o hives (itchy bumps)

- medication overuse headache. Some people who use too much migraine medicine, such as RizaFilm, for 10 or more days each month may have worse headaches (medication overuse headache). If your headaches get worse, your healthcare provider may decide to stop your treatment with RizaFilm.

- serotonin syndrome. A condition called serotonin syndrome can happen when Triptan medicines such as RizaFilm are taken with certain other medicines. Symptoms of serotonin syndrome may include:
  o agitation
  o hallucinations
  o coma
  o fast heartbeat
  o fast changes in your blood pressure
  o increased body temperature
  o muscle spasm
  o loss of coordination
  o nausea, vomiting or diarrhea

- increased blood pressure

The most common side effects of RizaFilm in adults include:

- having a lack of energy
- feeling sleepy or tired
- pain or pressure in your chest or throat
- dizziness
- nausea

Adverse reactions in children are expected to be similar to those in adults.

Tell your doctor if you have any side effect that bothers you or that does not go away.

If you take RizaFilm too often, this may result in you getting chronic (lasting a long time) headaches. In such cases, you should contact your doctor, as you may have to stop taking RizaFilm.

These are not all the possible side effects of RizaFilm. For more information, ask your doctor or pharmacist.

Call your doctor for medical advice about side effects. You may report side effects to Gensco Pharma at 1-866-608-6284 or FDA at 1-800-FDA-1088.

How should I store RizaFilm?

- Store RizaFilm at room temperature between 68°F to 77°F (20°C to 25°C).
- Keep RizaFilm in its aluminum pouch until you are ready to take it.

Keep RizaFilm and all medicines out of the reach of children.

General information about the safe and effective use of RizaFilm.

Medicines are sometimes prescribed for purposes other than those listed in a Patient Information leaflet. Do not use RizaFilm for a condition for which it was not prescribed. Do not give RizaFilm to other people, even if they have the same symptoms that you have. It may harm them.

You can ask your pharmacist or doctor for information about RizaFilm that is written for health professionals.

What are the ingredients in RizaFilm

Active ingredient in RizaFilm: rizatriptan.

Inactive ingredients in RizaFilm: ammonium glycyrrhizate, butylated hydroxytoluene, copovidone, cupric chloride, ethylcellulose, FD&C Blue No. 1, hydroxypropyl cellulose, isopropyl alcohol, levomenthol, methyl ethyl ketone, sodium acetate, sucralose, titanium dioxide, and triacetin.

RizaFilm Oral Films are manufactured by:
IntelGenx Corp.
Saint-Laurent, Quebec, H4S 1Y2 Canada

RizaFilm Oral Films are manufactured for:
Gensco Pharma
Doral, FL, 33122

The brands listed are the trademarks of their respective owners.

This Patient Information has been approved by the U.S. Food and Drug Administration. Issued: 12/2023

PRINCIPAL DISPLAY PANEL - 1 pouch and carton box with 18 pouches

NDC 35781-0600-1

RizaFilm

[rizatriptan]
oral film
10 mg

1 Film

Rx only

Gensco Pharma

NDC 35781-0600-8

18 Films

RizaFilm

[rizatriptan]
oral film
10 mg

Rx only

Contains 10mg rizatriptan equivalent to 14.53mg rizatriptan benzoate

Gensco Pharma